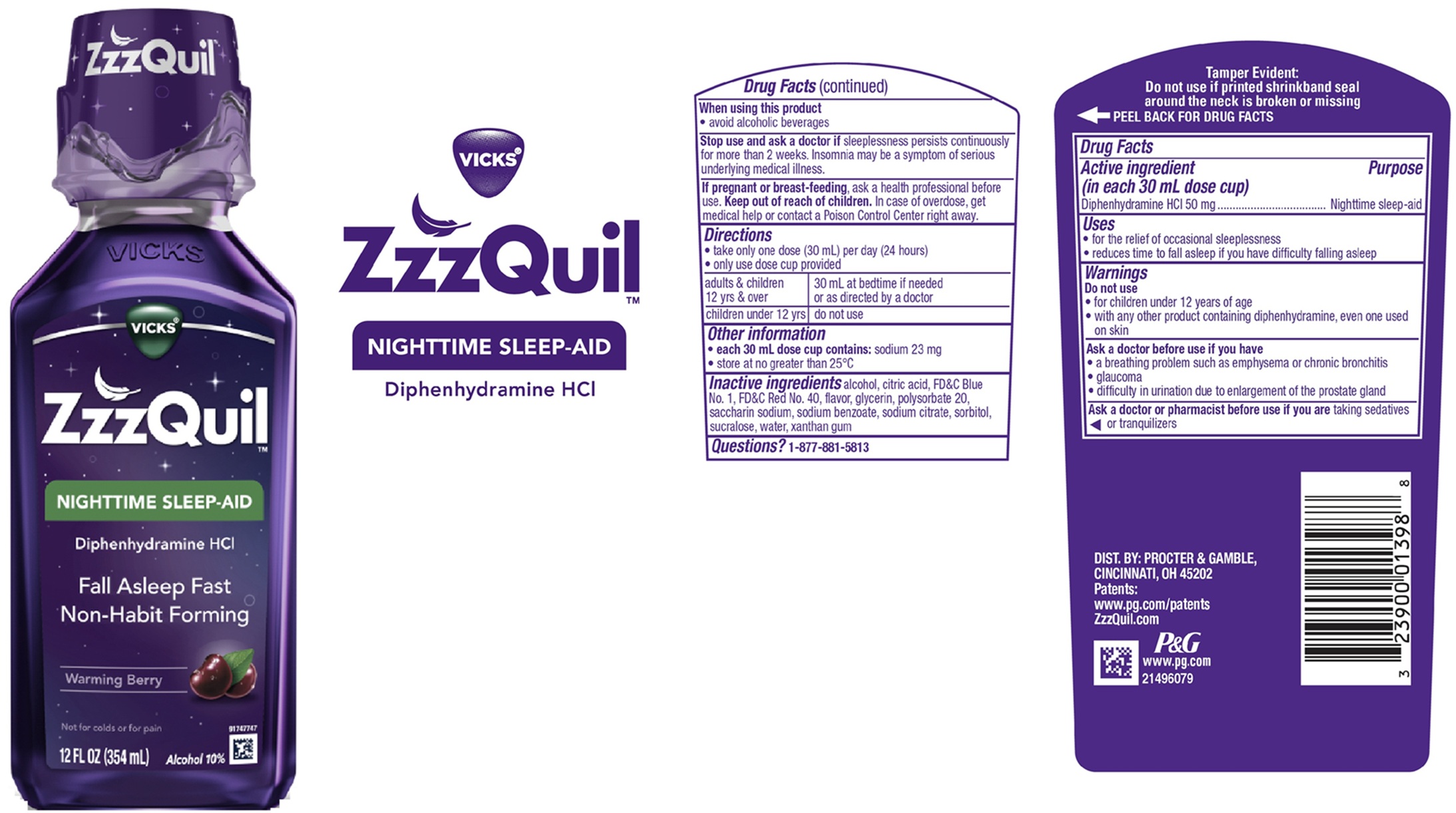 DRUG LABEL: ZzzQuil
NDC: 37000-500 | Form: LIQUID
Manufacturer: The Procter & Gamble Manufacturing Company
Category: otc | Type: HUMAN OTC DRUG LABEL
Date: 20260220

ACTIVE INGREDIENTS: DIPHENHYDRAMINE HYDROCHLORIDE 50 mg/30 mL
INACTIVE INGREDIENTS: CITRIC ACID MONOHYDRATE; GLYCERIN; POLYSORBATE 20; SODIUM CITRATE, UNSPECIFIED FORM; SORBITOL; SUCRALOSE; XANTHAN GUM; ALCOHOL; FD&C BLUE NO. 1; FD&C RED NO. 40; WATER; SACCHARIN SODIUM; TRISODIUM CITRATE DIHYDRATE; SODIUM BENZOATE

ZzzQuil™ NIGHTTIME SLEEP-AID WARMING BERRY

Drug Facts

Active ingredient (in each 30 mL dose cup)

Diphenhydramine HCl 50 mg

Purpose

Nighttime sleep-aid

Uses

- for the relief of occasional sleeplessness
- reduces time to fall asleep if you have difficulty falling asleep

Warnings

Do not use

- for children under 12 years of age
- with any other product containing diphenhydramine, even one used on skin

Ask a doctor before use if you have

- a breathing problem such as emphysema or chronic bronchitis
- glaucoma
- difficulty in urination due to enlargement of the prostate gland

Ask a doctor or pharmacist before use if you aretaking sedatives or tranquilizers

When using this product

- avoid alcoholic beverages

Stop use and ask a doctor if

sleeplessness persists continuously for more than 2 weeks. Insomnia may be a symptom of serious underlying medical illness.

PREGNANCY OR BREAST FEEDING

If pregnant or breast-feeding, ask a health professional before use.

Keep out of reach of children.

OVERDOSAGE

In case of overdose, get medical help or contact a Poison Control Center right away.

Directions

• take only one dose (30 mL) per day (24 hours)
• only use dose cup provided

adults & children 12 yrs & over | 30 mL at bedtime if needed or as directed by a doctor
children under 12 yrs | do not use

Other information

- each 30 mL dose cup contains:sodium 23 mg
- store at no greater than 25°C

Inactive ingredients

alcohol, citric acid, FD&C Blue No. 1, FD&C Red No. 40, flavor, glycerin, polysorbate 20, saccharin sodium, sodium benzoate, sodium citrate, sorbitol, sucralose, water, xanthan gum

Questions?

1-877-881-5813

Tamper Evident: Do not use if printed shrinkband seal around the neck is broken or missing.

DIST. BY PROCTER & GAMBLE,

CINCINNATI, OH 45202

PRINCIPAL DISPLAY PANEL - 354 ml Bottle Label

VICKS®

ZzzQuil™

NIGHTTIME SLEEP-AID

Diphenhydramine HCl

Fall Asleep Fast

Non-Habit Forming

Warming Berry

Not for colds or for pain

Alcohol 10%

12 FL OZ (354 ml)